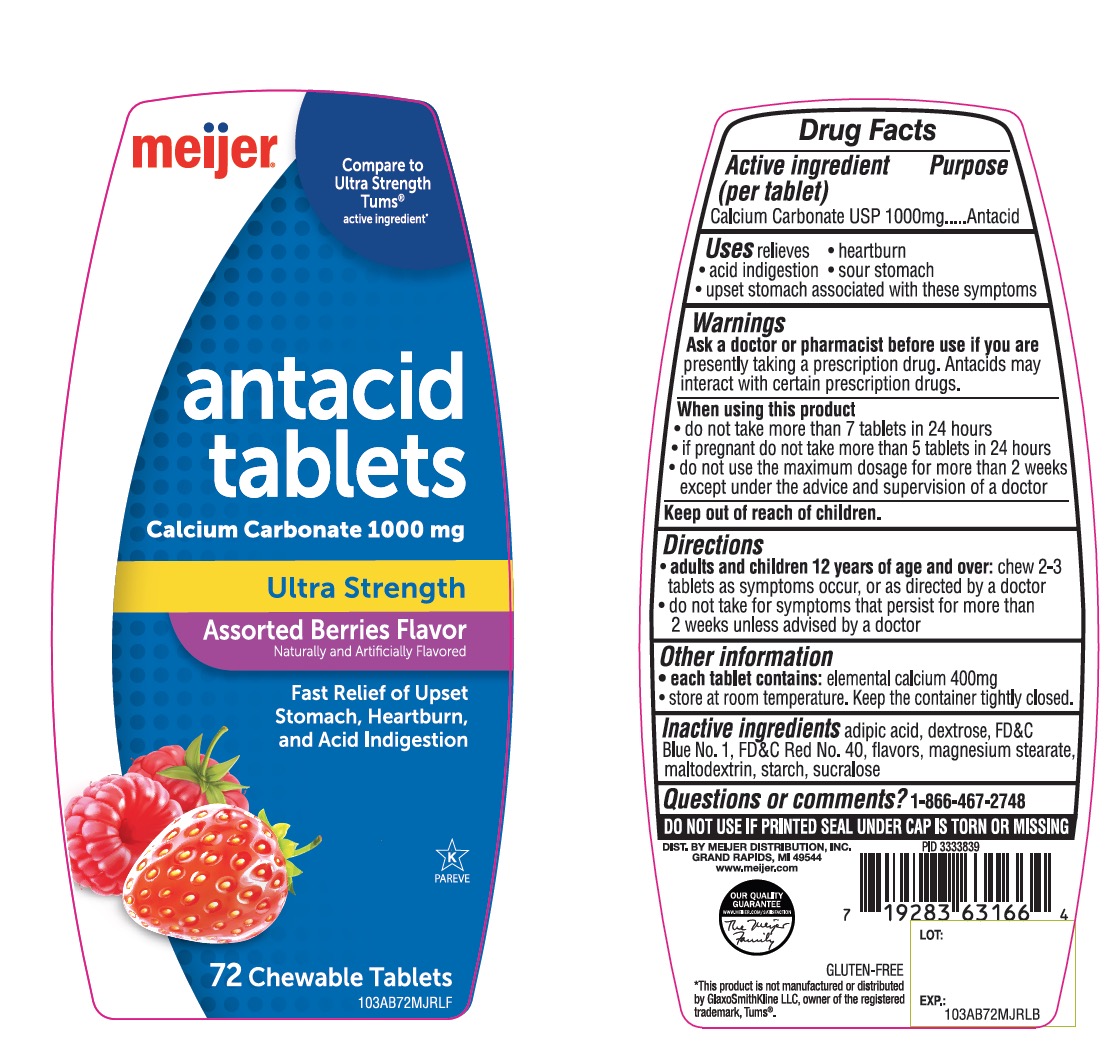 DRUG LABEL: Antacid
NDC: 41250-723 | Form: TABLET, CHEWABLE
Manufacturer: Meijer Distribution Inc
Category: otc | Type: HUMAN OTC DRUG LABEL
Date: 20251024

ACTIVE INGREDIENTS: CALCIUM CARBONATE 1000 mg/1 1
INACTIVE INGREDIENTS: ADIPIC ACID; DEXTROSE, UNSPECIFIED FORM; FD&C BLUE NO. 1; FD&C RED NO. 40; MAGNESIUM STEARATE; MALTODEXTRIN; STARCH, CORN; SUCRALOSE

Meijer Distribution, Inc. Antacid Tablets Drug Facts

Active ingredient (per tablet)

Calcium Carbonate USP 1000 mg

Purpose

Antacid

Uses

relieves

- heartburn
- sour stomach
- acid indigestion
- upset stomach associated with these symptoms

Warnings

Ask a doctor or pharmacist before use if you are

presently taking a prescription drug. Antacids may interact with certain prescription drugs.

When using this product

- do not take more than 7 tablets in 24 hours
- if pregnant do not take more than 5 tablets in 24 hours
- do not use the maximum dosage for more than 2 weeks except under the advice and supervision of a doctor

Directions

- adults and children 12 years of age and over:chew 2-3 tablets as symptoms occur, or as directed by a doctor
- do not take for symptoms that persist for more than 2 weeks unless advised by a doctor

Other information

- each tablet contains:calcium 400mg
- store at room temperature. Keep the container tightly closed.

Inactive ingredients

adipic acid, dextrose, FD&C Blue No. 1, FD&C Red No. 40, flavors, magnesium stearate, maltodextrin, starch, sucralose

Questions or Comments?

1-866-467-2748

Principal Display Panel

meijer®

NDC 41250-723-72

Compare to Ultra Strength Tums® active ingredient*

antacid tablets

Calcium Carbonate 1000 mg

Ultra Strength

Assorted Berries Flavor

Naturally and Artificially Flavored

Fast Relief of Upset Stomach, Heartburn, and Acid Indigestion

72 Chewable Tablets

K PAREVE

DO NOT USE IF PRINTED SEAL UNDER CAP IS TORN OR MISSING.

DIST. BY MEIJER DISTRIBUTION, INC.

GRAND RAPIDS, MI 49544

www.meijer.com

OUR QUALITY GURANTEE

WWW.MEIJER.COM/SATISFACTION

GLUTEN –FREE

This product is not manufactured or distributed by GlaxoSmithKline LLC Owner of the registered trademark, Tums®